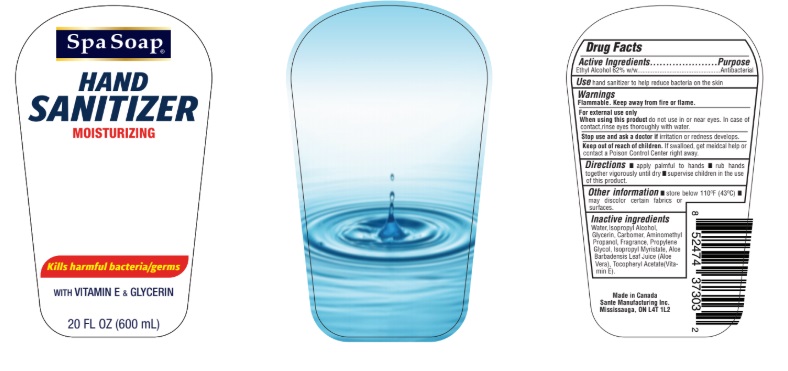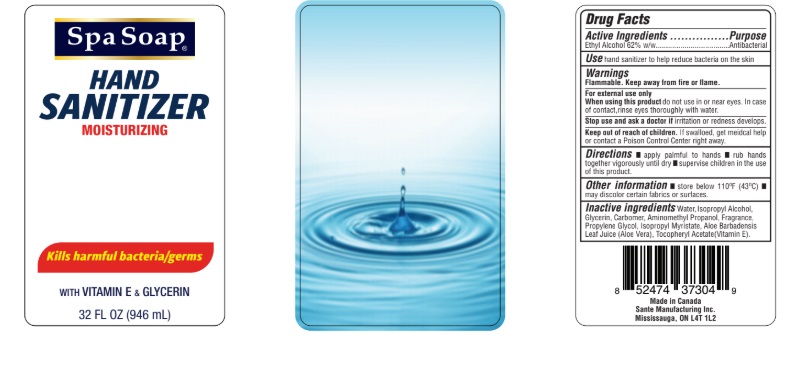 DRUG LABEL: Hand Sanitizer
NDC: 50157-501 | Form: GEL
Manufacturer: Brands International
Category: otc | Type: HUMAN OTC DRUG LABEL
Date: 20221212

ACTIVE INGREDIENTS: ALCOHOL 62 mL/100 mL
INACTIVE INGREDIENTS: CARBOMER COPOLYMER TYPE A; GLYCERIN; PROPYLENE GLYCOL; .ALPHA.-TOCOPHEROL ACETATE; AMINOMETHYLPROPANOL; ISOPROPYL MYRISTATE; ALOE; TROLAMINE; WATER

Spa Soap Hand Sanitizer: Moisturizing

Active Ingredient

Ethyl alcohol 62%.

Purpose

Antiseptic

INDICATIONS AND USAGE

For handwashing to decrease bacteria on the skin.

Warnings

Flammable, keep away from fire or flame. For external use only.

When using this product Avoid contact with eyes. In case of contact flush eyes with water.

Stop use and ask a doctor If redness or irritation develop and persist for more than 72 hours.

Keep out of reach of children. If swallowed get medical help or contact a Poison Control Center right away.

Directions

Spread on both hands, rub in, let dry.

INACTIVE INGREDIENT

Inactive Ingredients Carbomer, Fragrance, Glycerin, Propylene Glycol, Tocopheryl Acetate, Triethanolamine, Water, Isopropyl Myristate, Aminomethyl Propanol.